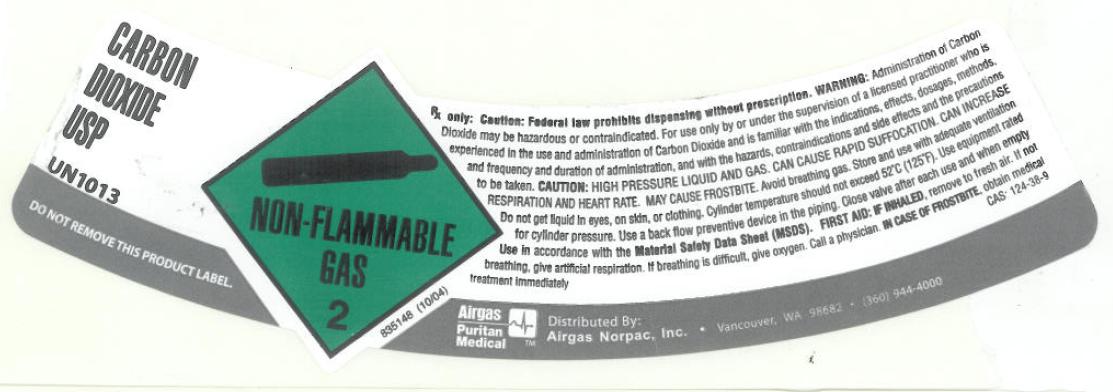 DRUG LABEL: Carbon Dioxide
NDC: 57472-004 | Form: GAS
Manufacturer: AIRGAS NOR PAC INC
Category: prescription | Type: HUMAN PRESCRIPTION DRUG LABEL
Date: 20110510

ACTIVE INGREDIENTS: Carbon Dioxide 992 mL/1 L

carbon dioxide

PACKAGE LABEL

CARBON DIOXIDE USP UN1013
DO NOT REMOVE THIS PRODUCT LABEL. NON-FLAMMABLE GAS 2 835148 (10/04)
Rx only. CAUTION: Federal law prohibits dispensing without prescription. WARNING: Administration of Carbon Dioxide may be hazardous or contraindicated. For use only by or under supervision of a licensed practitioner who is experienced in the use and administration of Carbon Dioxide and is familiar with the indications, effects, dosages, methods, and frequency and duration of administration, and with the hazards, contraindications, and side effects and the precautions to be taken. CAUTION: HIGH PRESSURE LIQUID AND GAS. CAN CAUSE RAPID SUFFOCATION. CAN INCREASE RESPIRATION AND HEART RATE. MAY CAUSE FROSTBITE. Avoid breathing gas. Store and use with adequate ventilation. Do not get liquid in eyes, on skin, and clothing. Cylinder temperatures should not exceed 52C (125F). Use equipment rated for cylinder pressure. Use a back flow preventive device in the piping. Close valve after each use and when empty. Use in accordance with the Material Safety Data Sheet (MSDS). FIRST AID: IF INHALED, remove to fresh air. If not breathing, give artificial respiration. If breathing is difficult, give oxygen. Call a physician. IN CASE OF FROSTBITE, obtain medical treatment immediately. CAS: 124-38-9
Airgas Puritan Medical TM Distributed by: Airgas Norpac, Inc. Vancouver, WA 98682 (360) 944-4000